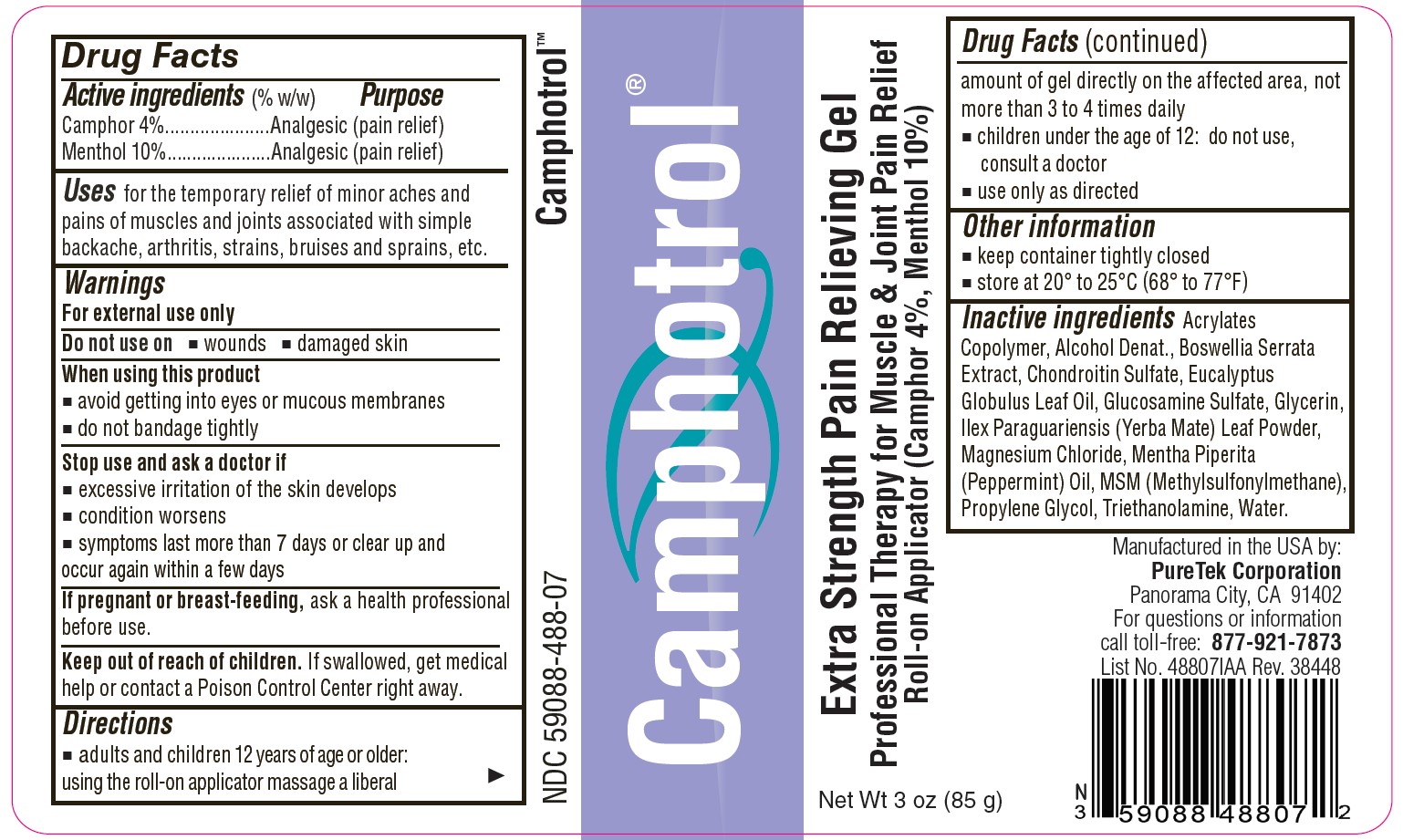 DRUG LABEL: Camphotrol
NDC: 59088-488 | Form: GEL
Manufacturer: PureTek Corporation
Category: otc | Type: HUMAN OTC DRUG LABEL
Date: 20240726

ACTIVE INGREDIENTS: CAMPHOR (SYNTHETIC) 4 g/100 g; MENTHOL 10 g/100 g
INACTIVE INGREDIENTS: METHACRYLIC ACID - ETHYL ACRYLATE COPOLYMER (4500 MPA.S); ALCOHOL; INDIAN FRANKINCENSE; CHONDROITIN SULFATE (BOVINE); EUCALYPTUS OIL; GLUCOSAMINE SULFATE; GLYCERIN; ILEX PARAGUARIENSIS LEAF; MAGNESIUM CHLORIDE; PEPPERMINT OIL; DIMETHYL SULFONE; PROPYLENE GLYCOL; TROLAMINE; WATER

Camphotrol®
Extra Strength Pain Relieving Gel Roll-on Applicator
Professional Therapy for Muscle & Joint Pain Relief

Active Ingredients (% by weight)

Camphor 4%

Menthol 10%

Purpose

Analgesic (pain relief)

Uses

for the temporary relief of minor aches and pains of muscles and joints associated with simple backache, arthritis, strains, bruises and sprains, etc.

Warnings

For external use only

Do not use on

■ wounds ■ damaged skin

When using this product

■ avoid getting into eyes or mucous membranes ■ do not bandage tightly

Stop use and ask a doctor if

■ excessive irritation of the skin develops ■ condition worsens
■ symptoms last more than 7 days or clear up and occur again within a few days

If pregnant or breast-feeding,

ask a health professional before use.

Keep out of reach of children.

If swallowed, get medical help or contact a Poison Control Center right away.

Directions

■ adults and children 12 years of age or older: using the roll-on applicator massage a liberal amount of gel directly on the affected area, not more than 3 to 4 times daily
■ children under the age of 12: do not use, consult a doctor ■ use only as directed

Other information

■ keep container tightly closed ■ store at 20° to 25°C (68° to 77°F)

Inactive ingredients

Acrylates Copolymer, Alcohol Denat., Boswellia Serrata Extract, Chondroitin Sulfate, Eucalyptus Globulus Leaf Oil, Glucosamine Sulfate, Glycerin, Ilex Paraguariensis (Yerba Mate) Leaf Powder, Magnesium Chloride, Mentha Piperita (Peppermint) Oil, MSM (Methylsulfonylmethane), Propylene Glycol, Triethanolamine, Water.